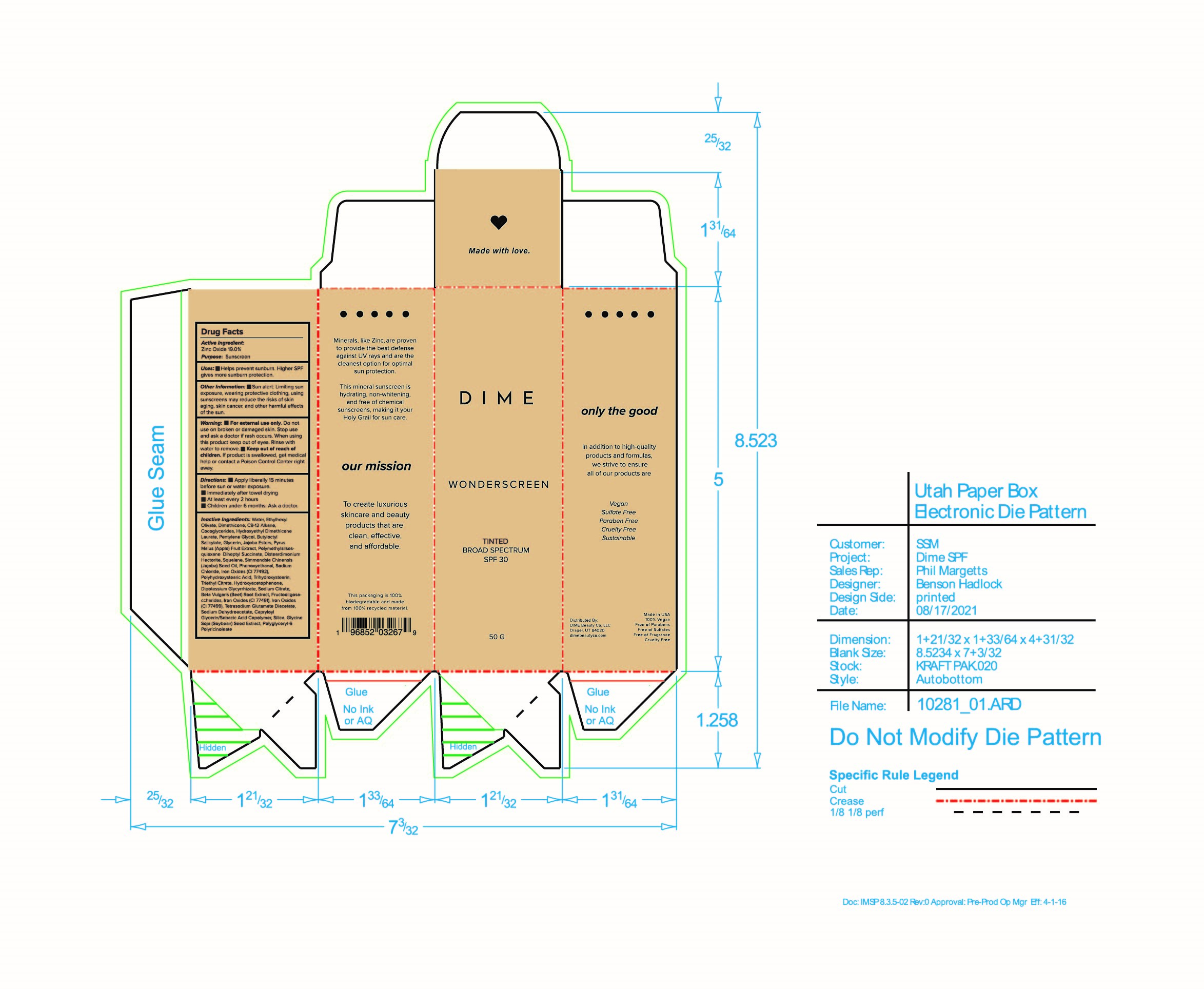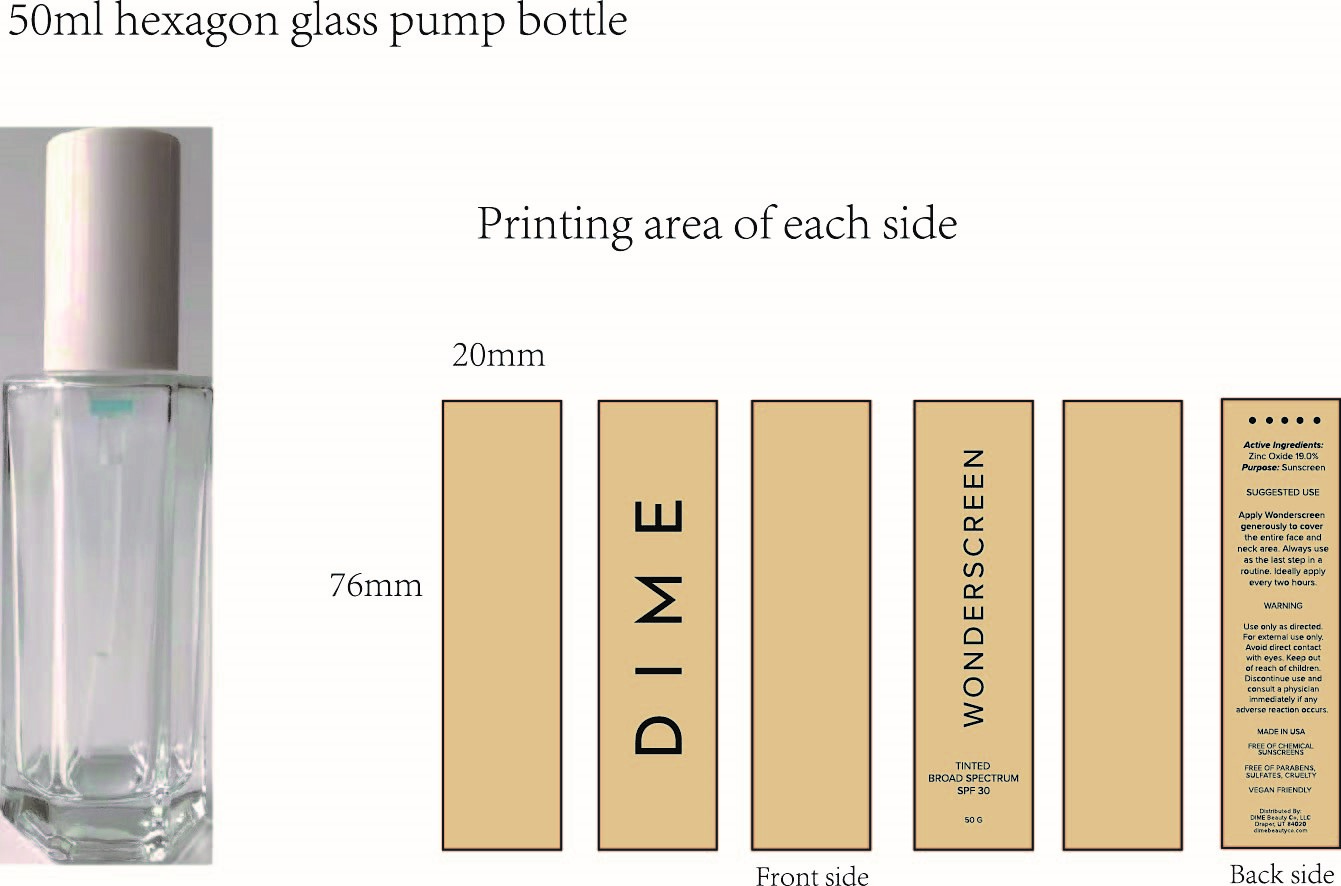 DRUG LABEL: Wonderscreen Tinted Broad Spectrum SPF 30
NDC: 82870-005 | Form: CREAM
Manufacturer: Dime Beauty Co, LLC
Category: otc | Type: HUMAN OTC DRUG LABEL
Date: 20251001

ACTIVE INGREDIENTS: ZINC OXIDE 19 g/100 g
INACTIVE INGREDIENTS: SILICON DIOXIDE; CAPRYLOYL GLYCERIN/SEBACIC ACID COPOLYMER (2000 MPA.S); SODIUM CITRATE; SOYBEAN; APPLE; DISTEARDIMONIUM HECTORITE; BEET; GLYCERIN; TRIETHYL CITRATE; GLYCYRRHIZINATE DIPOTASSIUM; SQUALANE; DIHEPTYL SUCCINATE; POLYGLYCERYL-6 POLYRICINOLEATE; PHENOXYETHANOL; FERRIC OXIDE YELLOW; JOJOBA OIL; POLYHYDROXYSTEARIC ACID (2300 MW); FERRIC OXIDE RED; FERROSOFERRIC OXIDE; TRIHYDROXYSTEARIN; TETRASODIUM GLUTAMATE DIACETATE; HYDROXYACETOPHENONE; PENTYLENE GLYCOL; SODIUM CHLORIDE; WATER; DIMETHICONE; COCO-GLYCERIDES; BUTYLOCTYL SALICYLATE; JOJOBA OIL, RANDOMIZED; POLYMETHYLSILSESQUIOXANE (11 MICRONS); SODIUM DEHYDROACETATE

Wonderscreen Tinted Broad Spectrum 30

Active Ingredient: Zinc Oxide 19.0%

Purpose: Sunscreen

Uses:

- Helps prevent sunburn. Higher SPF gives more sunburn protection.

Keep out of reach of children. If product is swallowed, get medical help or contact a Poison Control Center right away.

Stop use and ask a doctor if rash occurs.

Warning:

- For external use only. Do not use on broken or damaged skin. When using this product keep out of eyes. Rinse with water to remove.

Directions:

- Apply Liberally 15 minutes before sun or water exposure
- Immediately after towel drying
- At least every 2 hours
- Children under 6 months: Ask a doctor.

INACTIVE INGREDIENT

Inactive Ingredients: Water, Ethylhexyl Olivate, Dimethicone, C9-12 Alkane, Cocoglycerides, Hydroxyethyl Dimethicone Laurate, Pentylene Glycol, Butyloctyl Salicylate, Glycerin, Jojoba Esters, Pyrus Malus (Apple) Fruit Extract, Polymethylsilsesquioxane Diheptyl Succinate , Disteardimonium Hectorite, Squalane, Simmondisa (Jojoba) Seed Oil, Phenoxyethanol, Sodiium Chloride, Iron Oxides (CI 77492), Polyhydroxystearic Acid, Trihydroxystearin, Triethyl Citrate, Hydroxyacetophenone, Dipotassium Glycyrrhizate, Sodium Citrate, Beta Vulgaris (Beet) Root Extract Fructooligosaccharides, Iron Oxides (CI 77491), Iron oxides (CI 77499), Tetrasodium Glutamate Diacetate, Sodium Dehydroacetate, Capryloyl Glycerin/Sebacic Acid Copolymer, Silica, Glycine Soja (Soybean) Seed Extract, Polyglyceryl-6 Polyricinoleate

PACKAGE LABEL

Dime

Wonderscreen

Tinted Broad Spectrum SPF 30

50 G